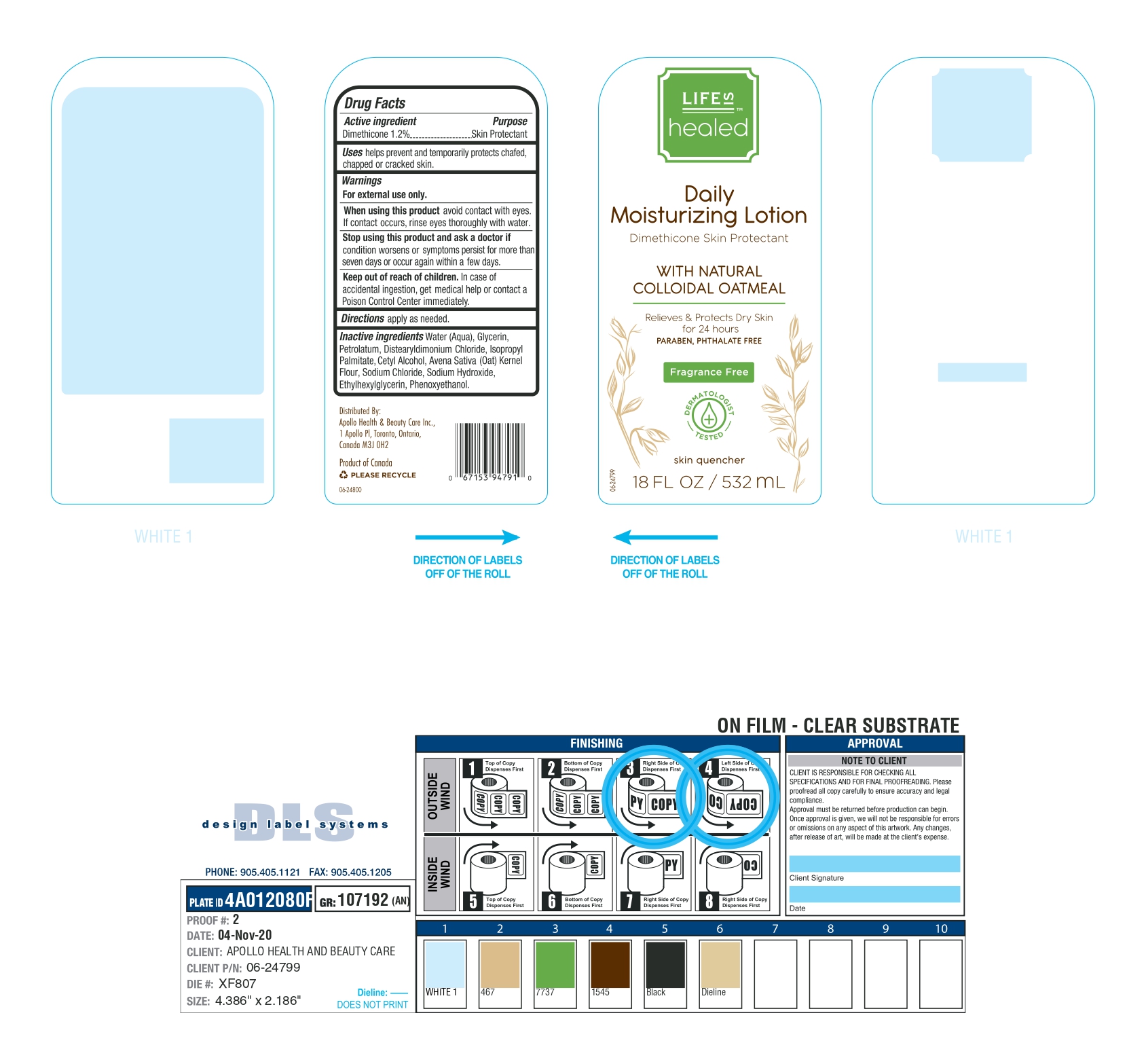 DRUG LABEL: Life is healed
NDC: 63148-028 | Form: LOTION
Manufacturer: Apollo Health and Beauty Care
Category: otc | Type: HUMAN OTC DRUG LABEL
Date: 20241020

ACTIVE INGREDIENTS: DIMETHICONE 12 mg/1 mL
INACTIVE INGREDIENTS: WATER; GLYCERIN; PETROLATUM; DISTEARYLDIMONIUM CHLORIDE; ISOPROPYL PALMITATE; CETYL ALCOHOL; OATMEAL; SODIUM CHLORIDE; SODIUM HYDROXIDE; ETHYLHEXYLGLYCERIN; PHENOXYETHANOL

63148-028-05, life is healed

Active Ingredient.

Dimethicone (1.2%)

Purpose

Skin Protectant

Uses

helps prevent and temporarily protects chafed, chapped or cracked skin.

Warnings

For external use only.

When using this product

Avoid contact with eyes. If contact occurs, rinse eyes thoroughly with water.

Stop using this product and ask a doctor if

condition worsens or symptoms persist for more than seven days or occur again within a few days.

Keep out of reach of children

In case of accidental ingestion, get medical help or contact a Poison Control Center immediately.

Directions

apply as needed.

Inactive Ingredients

Water (Aqua), Glycerin, Petrolatum, Distearyldimonium Chloride, Isopropyl Palmitate, Cetyl Alcohol, Avena Sativa (Oat) Kernel Flour, Sodium Chloride, Sodium Hydroxide, Ethylhexylglycerin, Phenoxyethanol.